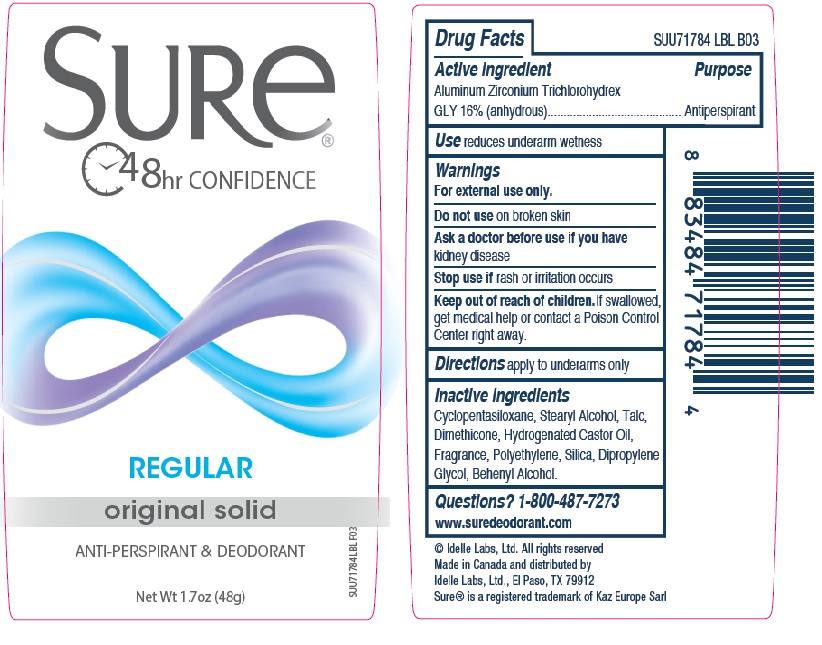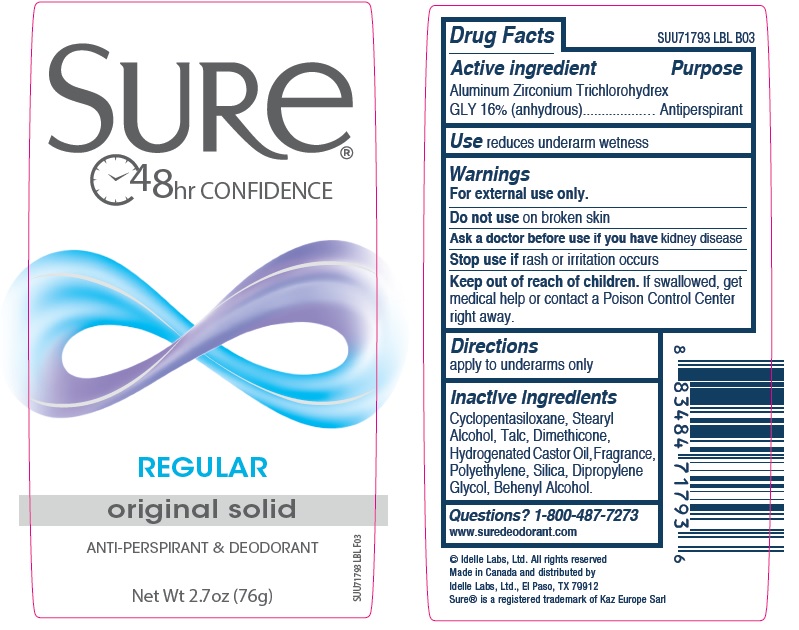 DRUG LABEL: Sure Original Solid Regular
NDC: 41595-5514 | Form: STICK
Manufacturer: Idelle Labs, Ltd
Category: otc | Type: HUMAN OTC DRUG LABEL
Date: 20210820

ACTIVE INGREDIENTS: ALUMINUM ZIRCONIUM TRICHLOROHYDREX GLY 16 g/100 g
INACTIVE INGREDIENTS: CYCLOMETHICONE 5; STEARYL ALCOHOL; TALC; DIMETHICONE; HYDROGENATED CASTOR OIL; HIGH DENSITY POLYETHYLENE; SILICON DIOXIDE; DIPROPYLENE GLYCOL; DOCOSANOL

Sure Original Solid Regular

SURe®
48hr CONFIDENCE
REGULAR
original solid
ANTI-PERSPIRANT & DEODORANT
Net Wt 1.7 oz (48g)

Drug Facts

Active ingredient

Aluminum Zirconium Trichlorohydrex GLY 16% (anhydrous)

Purpose

Antiperspirant

Use

Reduces underarm wetness

Warnings

For external use only.

Do not use

On broken skin

Ask a doctor before use if you have

Kidney disease

Stop use if

Rash or irritation occurs

Keep out of reach of children.

If swallowed, get medical help or contact a Poison Control Center right away.

Directions

Apply to underarms only

Inactive ingredients

Cyclopentasiloxane, Stearyl Alcohol, Talc, Dimethicone, Hydrogenated Castor Oil, Fragrance, Polyethylene, Silica, Dipropylene Glycol, Behenyl Alcohol.

Questions?

1-800-487-7273
www.suredeodorant.com
© Idelle Labs, Ltd. All rights reserved
Made in Canada and distributed by
Idelle Labs, Ltd., El Paso, TX 79912
Sure® is a registered trademark of Kaz Europe Sarl